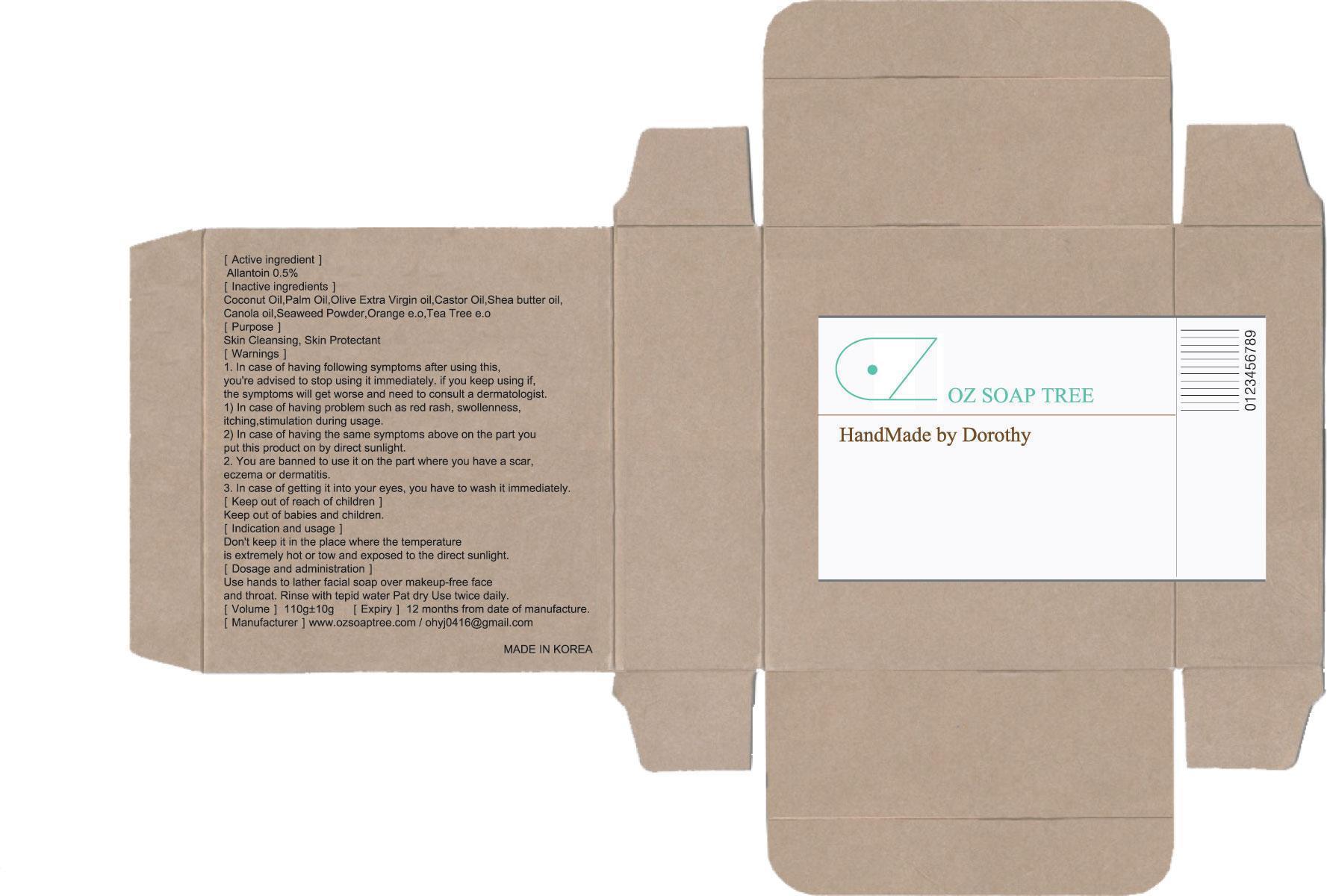 DRUG LABEL: OZ TREE
NDC: 58982-010 | Form: SOAP
Manufacturer: OZ SOAP TREE
Category: otc | Type: HUMAN OTC DRUG LABEL
Date: 20130519

ACTIVE INGREDIENTS: Allantoin 0.55 g/110 g
INACTIVE INGREDIENTS: COCONUT OIL; PALM OIL

ACTIVE INGREDIENT

Active ingredient: Allantoin 0.5%

INACTIVE INGREDIENT

Inactive ingredients: Coconut Oil, Palm Oil, Olive Extra Virgin Oil, Castor Oil, Shea Butter Oil, Canola Oil, Seaweed Powder, Orange e.o, Tea Tree e.o

PURPOSE

Purpose: Skin Cleansing, Skin Protectant

WARNINGS

1. In case of having following symptoms after using this, you're advised to stop using it immediately. If you keep using it, the symptoms will get worse and need to consult a dermatologist.
- In case of having problem such as red rash, swollenness, itching, stimulation during usage.
- In case of having the same symptoms above on the part you put this product on by direct sunlight.
2. You are banned to use it on the part where you have a scar, eczema or dermatitis.
3. In case of getting it into your eyes, you have to wash it immediately.

KEEP OUT OF REACH OF CHILDREN

Keep out of reach of babies and children.

INDICATIONS AND USAGE

Indication and usage:
Don't keep it in the place where the temperature is extremely hot or tow and exposed to the direct sunlight.

DOSAGE AND ADMINISTRATION

Use hands to lather facial soap over makeup free face and throat.
Rinse with tepid water. Pat dry. Use Twice daily.